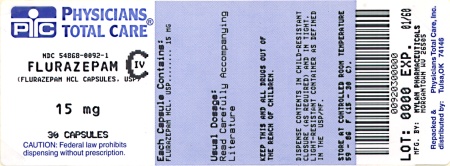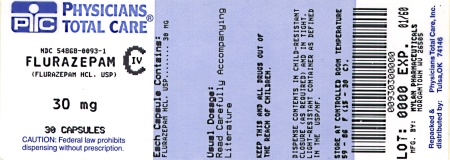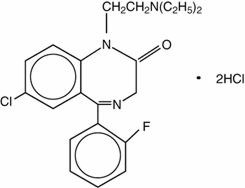 DRUG LABEL: Flurazepam Hydrochloride
NDC: 54868-0092 | Form: CAPSULE
Manufacturer: Physicians Total Care, Inc.
Category: prescription | Type: HUMAN PRESCRIPTION DRUG LABEL
Date: 20130603
DEA Schedule: CIV

ACTIVE INGREDIENTS: FLURAZEPAM HYDROCHLORIDE 15 mg/1 1
INACTIVE INGREDIENTS: SILICON DIOXIDE; MAGNESIUM STEARATE; CELLULOSE, MICROCRYSTALLINE; POWDERED CELLULOSE; SODIUM LAURYL SULFATE; FD&C BLUE NO. 1; FD&C RED NO. 3; GELATIN; TITANIUM DIOXIDE; FERROSOFERRIC OXIDE; D&C YELLOW NO. 10; FD&C BLUE NO. 2; FD&C RED NO. 40; PROPYLENE GLYCOL; SHELLAC

DESCRIPTION

Flurazepam hydrochloride is chemically 7-chloro-1-[2-(diethylamino)ethyl]-5-(o-fluoro-phenyl)-1,3dihydro-2H-1,4-benzodiazepin-2-one dihydrochloride. It is a pale yellow, crystalline compound, freely soluble in alcohol and very soluble in water. It has a molecular weight of 460.81 and the following structural formula:

Each capsule for oral administration contains either 15 mg or 30 mg of flurazepam hydrochloride, USP and the following inactive ingredients: colloidal silicon dioxide, magnesium stearate, microcrystalline cellulose, powdered cellulose and sodium lauryl sulfate. The empty gelatin capsule contains FD&C Blue No. 1, FD&C Red No. 3, gelatin and titanium dioxide.

The imprinting ink contains black iron oxide, D&C Yellow No. 10 Aluminum Lake, FD&C Blue No. 1 Aluminum Lake, FD&C Blue No. 2 Aluminum Lake, FD&C Red No. 40 Aluminum Lake, propylene glycol and shellac glaze.

CLINICAL PHARMACOLOGY

Flurazepam hydrochloride is rapidly absorbed from the G.I. tract. Flurazepam is rapidly metabolized and is excreted primarily in the urine. Following a single oral dose, peak flurazepam plasma concentrations ranging from 0.5 to 4.0 ng/mL occur at 30 to 60 minutes post-dosing. The harmonic mean apparent half-life of flurazepam is 2.3 hours. The blood level profile of flurazepam and its major metabolites was determined in man following the oral administration of 30 mg daily for 2 weeks. The N1-hydroxyethyl-flurazepam was measurable only during the early hours after a 30 mg dose and was not detectable after 24 hours. The major metabolite in blood was N1-desalkyl-flurazepam, which reached steady-state (plateau) levels after 7 to 10 days of dosing, at levels approximately 5- to 6-fold greater than the 24-hour levels observed on Day 1. The half-life of elimination of N1-desalkyl-flurazepam ranged from 47 to 100 hours. The major urinary metabolite is conjugated N1-hydroxyethyl-flurazepam which accounts for 22% to 55% of the dose. Less than 1% of the dose is excreted in the urine as N1-desalkyl-flurazepam.

This pharmacokinetic profile may be responsible for the clinical observation that flurazepam is increasingly effective on the second or third night of consecutive use and that for 1 or 2 nights after the drug is discontinued both sleep latency and total wake time may still be decreased.

Geriatric Pharmacokinetics

The single dose pharmacokinetics of flurazepam were studied in 12 healthy geriatric subjects (aged 61 to 85 years). The mean elimination half-life of desalkyl-flurazepam was longer in elderly male subjects (160 hours) compared with younger male subjects (74 hours), while mean elimination half-life was similar in geriatric female subjects (120 hours) and younger female subjects (90 hours). After multiple dosing, mean steady-state plasma levels of desalkyl-flurazepam were higher in elderly male subjects (81 ng/mL) compared with younger male subjects (53 ng/mL), while values were similar between elderly female subjects (85 ng/mL) and younger female subjects (86 ng/mL). The mean washout half-life of desalkyl-flurazepam was longer in elderly male and female subjects (126 and 158 hours, respectively) compared with younger male and female subjects (111 and 113 hours, respectively).^1

INDICATIONS AND USAGE

Flurazepam hydrochloride is a hypnotic agent useful for the treatment of insomnia characterized by difficulty in falling asleep, frequent nocturnal awakenings, and/or early morning awakening. Flurazepam hydrochloride capsules can be used effectively in patients with recurring insomnia or poor sleeping habits, and in acute or chronic medical situations requiring restful sleep. Sleep laboratory studies have objectively determined that flurazepam hydrochloride capsules are effective for at least 28 consecutive nights of drug administration. Since insomnia is often transient and intermittent, short-term use is usually sufficient. Prolonged use of hypnotics is usually not indicated and should only be undertaken concomitantly with appropriate evaluation of the patient.

CONTRAINDICATIONS

Flurazepam hydrochloride capsules are contraindicated in patients with known hypersensitivity to the drug.

Usage in Pregnancy

Benzodiazepines may cause fetal damage when administered during pregnancy. An increased risk of congenital malformations associated with the use of diazepam and chlordiazepoxide during the first trimester of pregnancy has been suggested in several studies.

Flurazepam hydrochloride is contraindicated in pregnant women. Symptoms of neonatal depression have been reported; a neonate whose mother received 30 mg of flurazepam hydrochloride nightly for insomnia during the 10 days prior to delivery appeared hypotonic and inactive during the first 4 days of life. Serum levels of N1-desalkyl-flurazepam in the infant indicated transplacental circulation and implicate this long-acting metabolite in this case. If there is a likelihood of the patient becoming pregnant while receiving flurazepam, she should be warned of the potential risks to the fetus. Patients should be instructed to discontinue the drug prior to becoming pregnant. The possibility that a woman of childbearing potential may be pregnant at the time of institution of therapy should be considered.

WARNINGS

Because sleep disturbances may be the presenting manifestation of a physical and/or psychiatric disorder, symptomatic treatment of insomnia should be initiated only after a careful evaluation of the patient. The failure of insomnia to remit after 7 to 10 days of treatment may indicate the presence of a primary psychiatric and/or medical illness that should be evaluated. Worsening of insomnia or the emergence of new thinking or behavior abnormalities may be the consequence of an unrecognized psychiatric or physical disorder. Such findings have emerged during the course of treatment with sedative-hypnotic drugs. Because some of the important adverse effects of sedative-hypnotics appear to be dose related (see PRECAUTIONS and DOSAGE AND ADMINISTRATION), it is important to use the smallest possible effective dose, especially in the elderly.

Complex behaviors such as “sleep-driving” (i.e., driving while not fully awake after ingestion of a sedative-hypnotic, with amnesia for the event) have been reported. These events can occur in sedative-hypnotic-naïve as well as in sedative-hypnotic-experienced persons. Although behaviors such as sleep-driving may occur with sedative-hypnotics alone at therapeutic doses, the use of alcohol and other CNS depressants with sedative-hypnotics appears to increase the risk of such behaviors, as does the use of sedative-hypnotics at doses exceeding the maximum recommended dose. Due to the risk to the patients and the community, discontinuation of sedative-hypnotics should be strongly considered for patients who report a “sleep-driving” episode. Other complex behaviors (e.g., preparing and eating food, making phone calls or having sex) have been reported in patients who are not fully awake after taking a sedative-hypnotic. As with sleep-driving, patients usually do not remember these events.

Severe Anaphylactic and Anaphylactoid Reactions

Rare cases of angioedema involving the tongue, glottis or larynx have been reported in patients after taking the first or subsequent doses of sedative-hypnotics, including flurazepam. Some patients have had additional symptoms such as dyspnea, throat closing, or nausea and vomiting that suggest anaphylaxis. Some patients have required medical therapy in the emergency department. If angioedema involves the tongue, glottis or larynx, airway obstruction may occur and be fatal. Patients who develop angioedema after treatment with flurazepam should not be rechallenged with the drug.

Patients receiving flurazepam hydrochloride should be cautioned about possible combined effects with alcohol and other CNS depressants. Also, caution patients that an additive effect may occur if alcoholic beverages are consumed during the day following the use of flurazepam hydrochloride for nighttime sedation. The potential for this interaction continues for several days following discontinuance of flurazepam, until serum levels of psychoactive metabolites have declined.

Patients should also be cautioned about engaging in hazardous occupations requiring complete mental alertness such as operating machinery or driving a motor vehicle after ingesting the drug, including potential impairment of the performance of such activities which may occur the day following ingestion of flurazepam hydrochloride.

Usage in Children

Clinical investigations of flurazepam hydrochloride have not been carried out in children. Therefore, the drug is not currently recommended for use in persons under 15 years of age.

Withdrawal symptoms of the barbiturate type have occurred after the discontinuation of benzodiazepines (see DRUG ABUSE AND DEPENDENCE).

PRECAUTIONS

Since the risk of the development of oversedation, dizziness, confusion and/or ataxia increases substantially with larger doses in elderly and debilitated patients, it is recommended that in such patients the dosage be limited to 15 mg. If flurazepam hydrochloride is to be combined with other drugs having known hypnotic properties or CNS-depressant effects, due consideration should be given to potential additive effects.

The usual precautions are indicated for severely depressed patients or those in whom there is any evidence of latent depression; particularly the recognition that suicidal tendencies may be present and protective measures may be necessary.

The usual precautions should be observed in patients with impaired renal or hepatic function and chronic pulmonary insufficiency.

Information for Patients“Sleep-Driving” and Other Complex Behavior

There have been reports of people getting out of bed after taking a sedative-hypnotic and driving their cars while not fully awake, often with no memory of the event. If a patient experiences such an episode, it should be reported to his or her doctor immediately, since “sleep-driving” can be dangerous. This behavior is more likely to occur when sedative-hypnotics are taken with alcohol or other central nervous system depressants (see WARNINGS). Other complex behaviors (e.g., preparing and eating food, making phone calls or having sex) have been reported in patients who are not fully awake after taking a sedative-hypnotic. As with sleep-driving, patients usually do not remember these events.

To assure the safe and effective use of benzodiazepines, patients should be informed that since benzodiazepines may produce psychological and physical dependence, it is advisable that they consult with their physician before either increasing the dose or abruptly discontinuing this drug.

Geriatric Use

Since the risk of the development of oversedation, dizziness, confusion and/or ataxia increases substantially with larger doses in elderly and debilitated patients, it is recommended that in such patients the dosage be limited to 15 mg. Staggering and falling have also been reported, particularly in geriatric patients.

Following single-dose administration of flurazepam, the elimination half-life for desalkyl-flurazepam was longer in elderly male subjects compared with younger male subjects, while values between elderly and young females were not significantly different. After multiple dosing, elimination half-life of desalkyl-flurazepam was longer in all elderly subjects compared with younger subjects, and mean steady-state serum concentrations were higher only in elderly male subjects relative to younger subjects (see CLINICAL PHARMACOLOGY: Geriatric Pharmacokinetics).

ADVERSE REACTIONS

Dizziness, drowsiness, light-headedness, staggering, ataxia and falling have occurred, particularly in elderly or debilitated persons. Severe sedation, lethargy, disorientation and coma, probably indicative of drug intolerance or overdosage, have been reported.

Also reported were headache, heartburn, upset stomach, nausea, vomiting, diarrhea, constipation, gastrointestinal pain, nervousness, talkativeness, apprehension, irritability, weakness, palpitations, chest pains, body and joint pains and genitourinary complaints. There have also been rare occurrences of leukopenia, granulocytopenia, sweating, flushes, difficulty in focusing, blurred vision, burning eyes, faintness, hypotension, shortness of breath, pruritus, skin rash, dry mouth, bitter taste, excessive salivation, anorexia, euphoria, depression, slurred speech, confusion, restlessness, hallucinations and elevated SGOT, SGPT, total and direct bilirubins, and alkaline phosphatase. Paradoxical reactions, e.g., excitement, stimulation and hyperactivity, have also been reported in rare instances.

DRUG ABUSE AND DEPENDENCE

Abuse and addiction are separate and distinct from physical dependence and tolerance. Abuse is characterized by misuse of the drug for non-medical purposes, often in combination with other psychoactive substances. Physical dependence is a state of adaptation that is manifested by a specific withdrawal syndrome that can be produced by abrupt cessation, rapid dose reduction, decreasing blood level of the drug and/or administration of an antagonist. Tolerance is a state of adaptation in which exposure to a drug induces changes that result in a diminution of one or more of the drug’s effects over time. Tolerance may occur to both the desired and undesired effects of the drug and may develop at different rates for different effects.

Addiction is a primary, chronic, neurobiological disease with genetic, psychosocial, and environmental factors influencing its development and manifestations. It is characterized by behaviors that include one or more of the following: impaired control over drug use, compulsive use, continued use despite harm, and craving. Drug addiction is a treatable disease, utilizing a multidisciplinary approach, but relapse is common.

Withdrawal symptoms, similar in character to those noted with barbiturates and alcohol (convulsions, tremor, abdominal and muscle cramps, vomiting and sweating), have occurred following abrupt discontinuance of benzodiazepines. The more severe withdrawal symptoms have usually been limited to those patients who had received excessive doses over an extended period of time. Generally milder withdrawal symptoms (e.g., dysphoria and insomnia) have been reported following abrupt discontinuance of benzodiazepines taken continuously at therapeutic levels for several months. Consequently, after extended therapy, abrupt discontinuation should generally be avoided and a gradual dosage tapering schedule followed. Addiction-prone individuals (such as drug addicts or alcoholics) should be under careful surveillance when receiving flurazepam hydrochloride or other psychotropic agents because of the predisposition of such patients to habituation and dependence.

OVERDOSAGE

Manifestations of flurazepam hydrochloride overdosage include somnolence, confusion and coma. Respiration, pulse and blood pressure should be monitored as in all cases of drug overdosage. General supportive measures should be employed, along with immediate gastric lavage. Intravenous fluids should be administered and an adequate airway maintained. Hypotension and CNS depression may be combated by judicious use of appropriate therapeutic agents. The value of dialysis has not been determined. If excitation occurs in patients following flurazepam hydrochloride overdosage, barbiturates should not be used. As with the management of intentional overdosage with any drug, it should be borne in mind that multiple agents may have been ingested.

Flumazenil, a specific benzodiazepine-receptor antagonist, is indicated for the complete or partial reversal of the sedative effects of benzodiazepines and may be useful in situations when an overdose with a benzodiazepine is known or suspected. Prior to the administration of flumazenil, necessary measures should be instituted to secure airway, ventilation, and intravenous access. Flumazenil is intended as an adjunct to, not as a substitute for, proper management of benzodiazepine overdose. Patients treated with flumazenil should be monitored for resedation, respiratory depression, and other residual benzodiazepine effects for an appropriate period after treatment. The prescriber should be aware of a risk of seizure in association with flumazenil treatment, particularly in long-term benzodiazepine users and in cyclic antidepressant overdose. The complete flumazenil package insert including CONTRAINDICATIONS, WARNINGS, and PRECAUTIONS should be consulted prior to use.

DOSAGE AND ADMINISTRATION

Dosage should be individualized for maximal beneficial effects. The usual adult dosage is 30 mg before retiring. In some patients, 15 mg may suffice. In elderly and/or debilitated patients, 15 mg is usually sufficient for a therapeutic response and it is therefore recommended that therapy be initiated with this dosage.

HOW SUPPLIED

Flurazepam Hydrochloride Capsules, USP are available containing either 15 mg or 30 mg of flurazepam hydrochloride, USP.

The 15 mg capsule is a hard-shell gelatin capsule with a white opaque cap and a powder blue opaque body filled with off-white to yellow powder. The capsule is axially printed with MYLAN over 4415 in black ink on both the cap and body. They are available as follows:

Bottles of 20 | NDC 54868-0092-2
Bottles of 30 | NDC 54868-0092-1

The 30 mg capsule is a hard-shell gelatin capsule with a powder blue opaque cap and a powder blue opaque body filled with off-white to yellow powder. The capsule is axially printed with MYLAN over 4430 in black ink on both the cap and body. They are available as follows:

Bottles of 10 | NDC 54868-0093-0
Bottles of 30 | NDC 54868-0093-1

Store at 20° to 25°C (68° to 77°F). [See USP Controlled Room Temperature.]

Protect from light.

Dispense in a tight, light-resistant container as defined in the USP using a child-resistant closure.

PHARMACIST: Dispense a Medication Guide with each prescription.

REFERENCES

1. Greenblatt DJ, Divoll M, Hammatz JS, MacLauglin DS, Shader RI: Kinetics and clinical effects of flurazepam in young and elderly noninsomniacs. Clin Pharmacol Ther 30:475–486, 1981.

MEDICATION GUIDE FLURAZEPAM HYDROCHLORIDE CAPSULES, USP

Flurazepam Hydrochloride Capsules USP, 15 mg and 30 mg are a Sedative-Hypnotic Indicated for Insomnia

Read this Medication Guide carefully before you start taking your medicine and each time you get more, since there may be new information. It does not contain all the information about your medicine that you may need to know, so please ask your doctor, nurse or pharmacist if you have any questions.

IMPORTANT

YOUR DOCTOR HAS PRESCRIBED THIS DRUG FOR YOUR USE ONLY. DO NOT LET ANYONE ELSE USE IT. KEEP THIS MEDICINE OUT OF THE REACH OF CHILDREN AND PETS. If a child puts a flurazepam hydrochloride capsule in his or her mouth or swallows it, call your local Poison Control Center or go immediately to the nearest emergency room.

What is the most important information I should know about sedative-hypnotic drugs?

After taking a sedative-hypnotic drug, you may get up out of bed while not being fully awake and do an activity that you do not know you are doing. The next morning, you may not remember that you did anything during the night. You have a higher chance for doing these activities if you drink alcohol or take other medications that make you sleepy with a sedative-hypnotic drug.

Reported activities include:

- driving a car ("sleep-driving")
- making and eating food
- talking on the phone
- having sex
- sleep-walking

Important:

1. Take a sedative-hypnotic drug exactly as prescribed:
  - Do not take more sedative-hypnotic drugs than prescribed.
  - Take the sedative-hypnotic drug right before you get in bed, not sooner.
2. Do not take a sedative-hypnotic drug if you:
  - drink alcohol
  - take other medicines that can make you sleepy. Talk to your doctor about all of your medicines. Your doctor will tell you if you can take a sedative-hypnotic drug with your other medicines
  - cannot get a full night sleep
3. Call your doctor right away if you find out that you have done any of the above activities after taking a sedative-hypnotic drug.

What is flurazepam?

Flurazepam is a sedative-hypnotic agent used to treat insomnia (difficulty falling asleep and staying asleep).

Who should not take flurazepam?

Do not use flurazepam if you are:

- allergic to anything in flurazepam hydrochloride capsules. (Being allergic may include having a rash, itching, swelling or breathing difficulties.) See the end of this Medication Guide for a complete list of ingredients in flurazepam hydrochloride capsules. In rare cases patient have had additional symptoms such as shortness of breath, throat closing, or nausea and vomiting that suggest an allergic reaction. Some patients have required medical therapy in the emergency department as these rare complications could be fatal. Patients who experience these symptoms should seek medical attention and discontinue taking the sedative-hypnotic drug.
- pregnant or intending to become pregnant. If a woman becomes pregnant while taking flurazepam, she should discontinue use immediately.
- under 15 years of age. Flurazepam has not been studied in children.

How should I take flurazepam?

Flurazepam comes as a capsule to take by mouth. You should take flurazepam, or other sedative-hypnotic medications, exactly as directed by your doctor. It usually is taken right before you get in bed, not sooner. If you forget to take flurazepam at bedtime, you are unable to fall asleep, and you will still be able to stay in bed for a full night’s sleep, you may take flurazepam at that time. Do not take a double dose of flurazepam to make up for a missed dose.

The smallest possible effective dose is suggested for elderly patients due to the risk of the development of oversedation, dizziness, confusion and/or loss of coordination.

Sleep problems are often temporary, requiring treatment for a very short time. You should not use flurazepam, or any other sedative-hypnotic medications, for long periods of time without talking to your doctor about the risks and benefits of prolonged use.

In the case of a suspected overdose, you should contact your local poison control center immediately.

What should I avoid while taking flurazepam?

Do not drink alcohol or take other medications that depress the central nervous system.

While taking flurazepam, do not engage in any hazardous occupations requiring complete mental alertness such as operating machinery or driving a car.

What are the possible or reasonably likely side effects of flurazepam?

Dizziness, drowsiness, light-headedness, staggering, loss of coordination and falling have occurred, particularly in elderly or debilitated persons. Severe sedation, lethargy, disorientation and coma, probably indicative of drug intolerance or overdosage, have been reported. Also reported are headache, heartburn, upset stomach, nausea, vomiting, diarrhea, constipation, nervousness, talking more than usual, anxiety, irritability, weakness, pounding heartbeat, chest pain, body and joint pains and difficulty urinating.

Call your doctor for medical advice about side effects. You may report side effects to FDA at 1-800-FDA-1088.

General information about the safe and effective use of flurazepam hydrochloride capsules

Medicines are sometimes prescribed for purposes other than those listed in a Medication Guide. If you have any concerns about taking this, or any sedative-hypnotic medication, please ask your doctor. For detailed information regarding flurazepam hydrochloride capsules please consult the physician’s package insert. Do not use for conditions for which this medication was not prescribed. Do not give this medication to others.

What are the ingredients of flurazepam hydrochloride capsules, USP?

Active Ingredient: flurazepam hydrochloride, USP

Inactive Ingredients: colloidal silicon dioxide, magnesium stearate, microcrystalline cellulose, powdered cellulose and sodium lauryl sulfate. The empty gelatin capsule contains FD&C Blue No. 1, FD&C Red No. 3, gelatin and titanium dioxide. The imprinting ink contains black iron oxide, D&C Yellow No. 10 Aluminum Lake, FD&C Blue No. 1 Aluminum Lake, FD&C Blue No. 2 Aluminum Lake, FD&C Red No. 40 Aluminum Lake, propylene glycol and shellac glaze.

How should I store flurazepam hydrochloride capsules?

- Store flurazepam hydrochloride capsules at room temperature, 20° to 25°C (68° to 77°F).
- KEEP THIS MEDICINE OUT OF THE REACH OF CHILDREN. If a child accidentally takes flurazepam hydrochloride capsules, call your local Poison Control Center or go immediately to the nearest emergency room.

This Medication Guide has been approved by the U.S. Food and Drug Administration.

Mylan Pharmaceuticals Inc.
Morgantown, WV 26505

REVISED MAY 2010
FLZ:R16mmt/MG:FLZ:R1

Relabeling and Repackaging by:
Physicians Total Care, Inc.
Tulsa, OK 74146

PRINCIPAL DISPLAY PANEL

CIV

FLURAZEPAM
HYDROCHLORIDE
CAPSULES, USP
15 mg

PHARMACIST: Dispense the accompanying
Medication Guide to each patient.

(Rx only)

Each capsule contains:
Flurazepam
hydrochloride, USP. . . . 15 mg

Dispense in a tight, light-resistant
container as defined in the USP
using a child-resistant closure.

Keep container tightly closed.

Keep this and all medication out
of the reach of children.

Store at 20° to 25°C (68° to 77°F).
[See USP Controlled Room
Temperature.]

Protect from light.

Usual Adult Dosage: See accom-
panying prescribing information.

CIV

FLURAZEPAM
HYDROCHLORIDE
CAPSULES, USP
30 mg

PHARMACIST: Dispense the accompanying
Medication Guide to each patient.

(Rx only)

Each capsule contains:
Flurazepam
hydrochloride, USP. . . . 30 mg

Dispense in a tight, light-resistant
container as defined in the USP
using a child-resistant closure.

Keep container tightly closed.

Keep this and all medication out
of the reach of children.

Store at 20° to 25°C (68° to 77°F).
[See USP Controlled Room
Temperature.]

Protect from light.

Usual Adult Dosage: See accom-
panying prescribing information.